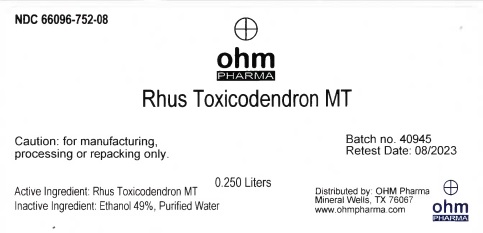 DRUG LABEL: Rhus Toxicodendron MT
NDC: 66096-752 | Form: TINCTURE
Manufacturer: OHM PHARMA INC.
Category: homeopathic | Type: HUMAN OTC DRUG LABEL
Date: 20211229

ACTIVE INGREDIENTS: TOXICODENDRON PUBESCENS LEAF 1 [hp_X]/0.25 L
INACTIVE INGREDIENTS: ALCOHOL; WATER

Rhus Toxicodendron MT

Active Ingredient: Rhus Toxicodendron MT

WARNINGS

Caution: for manufacturing,

processing or repacking only.

OTHER SAFETY INFORMATION

Batch no. 40945

Retest Date: 08/2023

Inactive Ingredient: Ethanol 49%, Purified Water

QUESTIONS

Distributed by: OHM Pharma

Mineral Wells, TX 76067

www.ohmpharma.com

PACKAGE LABEL

NDC 66096-752-08

Rhus Toxicodendron MT

0.250 Liters

Caution: for manufacturing,

processing or repacking only.

Active Ingredient: Rhus Toxicodendron MT

Inactive Ingredient: Ethanol 49%, Purified Water

Batch no. 40945

Retest Date: 08/2023

Distributed by: OHM Pharma

Mineral Wells, TX 76067

www.ohmpharma.com